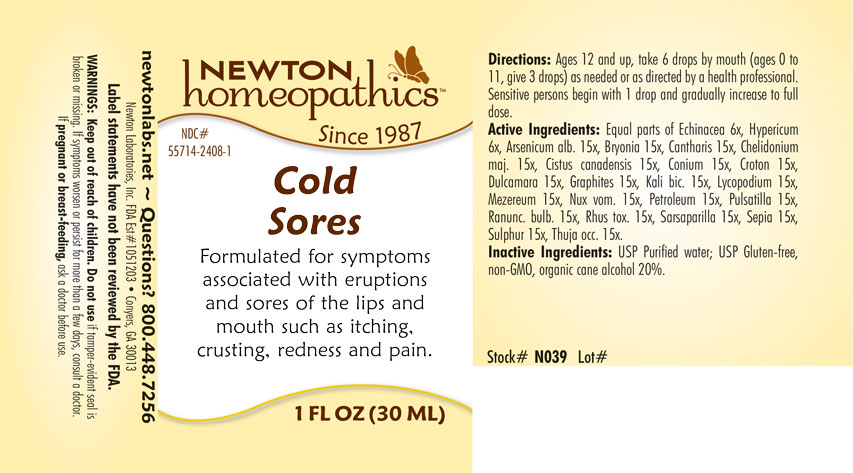 DRUG LABEL: Cold Sores
NDC: 55714-2408 | Form: LIQUID
Manufacturer: Newton Laboratories, Inc.
Category: homeopathic | Type: HUMAN OTC DRUG LABEL
Date: 20250206

ACTIVE INGREDIENTS: ARSENIC TRIOXIDE 15 [hp_X]/1 mL; BRYONIA ALBA ROOT 15 [hp_X]/1 mL; LYTTA VESICATORIA 15 [hp_X]/1 mL; CHELIDONIUM MAJUS 15 [hp_X]/1 mL; HELIANTHEMUM CANADENSE 15 [hp_X]/1 mL; CONIUM MACULATUM FLOWERING TOP 15 [hp_X]/1 mL; CROTON TIGLIUM SEED 15 [hp_X]/1 mL; SOLANUM DULCAMARA TOP 15 [hp_X]/1 mL; GRAPHITE 15 [hp_X]/1 mL; POTASSIUM DICHROMATE 15 [hp_X]/1 mL; LYCOPODIUM CLAVATUM SPORE 15 [hp_X]/1 mL; DAPHNE MEZEREUM BARK 15 [hp_X]/1 mL; STRYCHNOS NUX-VOMICA SEED 15 [hp_X]/1 mL; KEROSENE 15 [hp_X]/1 mL; ANEMONE PULSATILLA 15 [hp_X]/1 mL; RANUNCULUS BULBOSUS 15 [hp_X]/1 mL; TOXICODENDRON PUBESCENS LEAF 15 [hp_X]/1 mL; SMILAX ORNATA ROOT 15 [hp_X]/1 mL; SEPIA OFFICINALIS JUICE 15 [hp_X]/1 mL; SULFUR 15 [hp_X]/1 mL; THUJA OCCIDENTALIS LEAFY TWIG 15 [hp_X]/1 mL; ECHINACEA, UNSPECIFIED 6 [hp_X]/1 mL; HYPERICUM PERFORATUM 6 [hp_X]/1 mL
INACTIVE INGREDIENTS: ALCOHOL; WATER

ColdSo 2408L

INDICATIONS & USAGE SECTION

Formulated for symptoms associated with eruptions and sores of the lips and mouth such as itching, crusting, redness and pain.

DOSAGE & ADMINISTRATION SECTION

Directions: Ages 12 and up, take 6 drops by mouth (ages 0 to 11, give 3 drops) as needed or as directed by a health professional. Sensitive persons begin with 1 drop and gradually increase to full dose.

OTC - ACTIVE INGREDIENT SECTION

Equal parts of Echinacea 6x, Hypericum 6x, Arsenicum alb. 15x, Bryonia 15x, Cantharis 15x, Chelidonium majus 15x, Cistus canadensis 15x, Conium 15x, Croton 15x, Dulcamara 15x, Graphites 15x, Kali bic.15x, Lycopodium 15x, Mezereum 15x, Nux vom. 15x, Petroleum 15x, Pulsatilla 15x, Ranunc. bulb. 15x, Rhus toxicodendron 15x, Sarsaparilla 15x, Sepia 15x, Sulphur 15x, Thuja occ. 15x.

OTC - PURPOSE SECTION

Formulated for symptoms associated with eruptions and sores of the lips and mouth such as itching, crusting, redness and pain.

INACTIVE INGREDIENT SECTION

Inactive Ingredients: USP Purified Water; USP Gluten-free, non-GMO, organic cane alcohol 20%.

QUESTIONS SECTION

newtonlabs.net – Questions? 800.448.7256

Newton Laboratories, Inc. FDA Est # 1051203 - Conyers, GA 30013

WARNINGS SECTION

WARNINGS: Keep out of reach of children. Do not use if tamper-evident seal is broken or missing. If symptoms worsen or persist for more than a few days, consult a doctor. If pregnant or breast-feeding, ask a doctor before use.

OTC - PREGNANCY OR BREAST FEEDING SECTION

If pregnant or breast-feeding, ask a doctor before use.

OTC - KEEP OUT OF REACH OF CHILDREN SECTION

Keep out of reach of children.